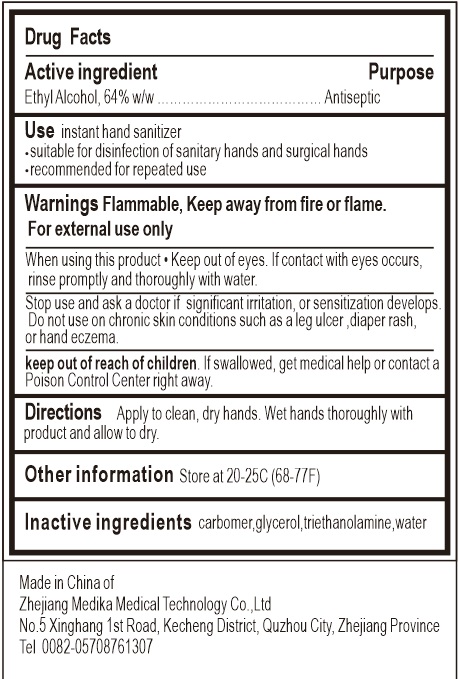 DRUG LABEL: YOGARDTM Hand Sanitizer
NDC: 78920-001 | Form: GEL
Manufacturer: Zhejiang Meijiahua Medical Technology Co., Ltd.
Category: otc | Type: HUMAN OTC DRUG LABEL
Date: 20200727

ACTIVE INGREDIENTS: ALCOHOL 64 mL/100 mL
INACTIVE INGREDIENTS: CARBOMER HOMOPOLYMER, UNSPECIFIED TYPE; WATER; TROLAMINE; GLYCERIN

78920-001 YOGARDTM Hand Sanitizer 64% Alcohol

Active Ingredient

Ethyl Alcohol 64%

Purpose

Antisepic

Use

instant hand sanitizer
.suitable for disinfection of sanitary hands and surgical hands
.recommended for repeated use

Warnings Flammable, Keep away from fire or flame.
For external use only
When using this product●Keep out of eyes. lfcontact with eyes occurs,
rinse promptly and thoroughly with water.
Stop use and ask a doctor if significant irtation, or sensitizaion develops.
Do notuse on chronic skin conditions such as a leg ulcer ,diaper rash,or hand eczema.

keep out of reach of children. If sallowed, get medical help or contact a Poison Control Center right away.

Directions

Directions Apply to clean, dry hands. Wet hands thoroughly with product and allow to dry.

Inactive ingredients

Aqua, Glycerol, Aloe Barbadensis Extract, Tocopheryl Acetate (Vitamin E), Carbomer, Triethanolamine